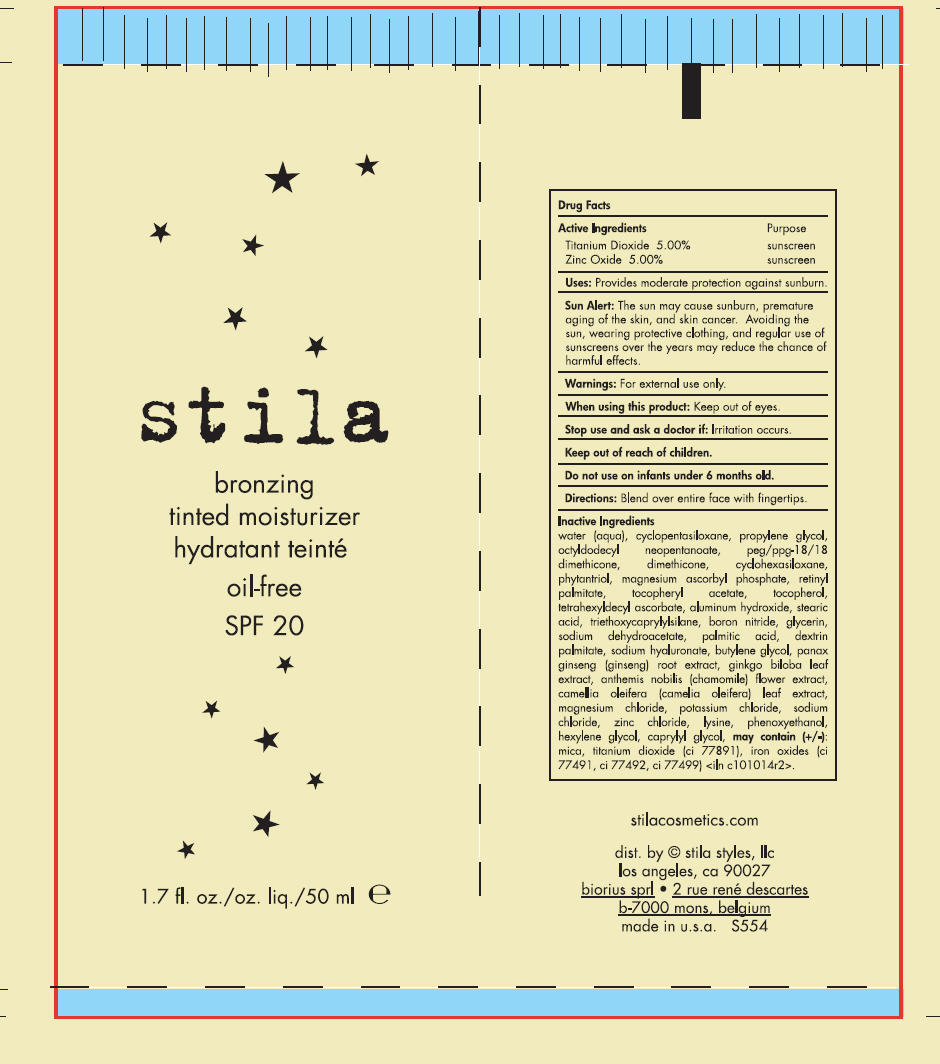 DRUG LABEL: stila bronzing tinted moisturizer oil-free SPF 20
NDC: 76049-554 | Form: LOTION
Manufacturer: Stila Styles, LLC
Category: otc | Type: HUMAN OTC DRUG LABEL
Date: 20131122

ACTIVE INGREDIENTS: Titanium Dioxide 50 mg/1 mL; Zinc Oxide 50 mg/1 mL
INACTIVE INGREDIENTS: water; cyclomethicone 5; propylene glycol; octyldodecyl neopentanoate; peg/ppg-18/18 dimethicone; dimethicone; cyclomethicone 6; phytantriol; magnesium ascorbyl phosphate; vitamin a palmitate; .alpha.-tocopherol acetate; tocopherol; tetrahexyldecyl ascorbate; aluminum hydroxide; stearic acid; triethoxycaprylylsilane; boron nitride; glycerin; sodium dehydroacetate; palmitic acid; hyaluronate sodium; butylene glycol; asian ginseng; ginkgo; chamaemelum nobile flower; camellia oleifera leaf; magnesium chloride; potassium chloride; sodium chloride; zinc chloride; lysine; phenoxyethanol; hexylene glycol; caprylyl glycol; mica; ferric oxide red; ferric oxide yellow; ferrosoferric oxide

stila bronzing tinted moisturizer oil-free SPF 20

Drug Facts

ACTIVE INGREDIENT

Active Ingredients | Purpose
Titanium Dioxide 5.00% | sunscreen
Zinc Oxide 5.00% | sunscreen

Uses

Provides moderate protection against sunburn.

Sun Alert

The sun may cause sunburn, premature aging of the skin, and skin cancer. Avoiding the sun, wearing protective clothing, and regular use of sunscreens over the years may reduce the chance of harmful effects.

Warnings

For external use only.

When using this product

Keep out of eyes.

Stop use and ask a doctor if

Irritation occurs.

Keep out of reach of children.

Do not use on infants under 6 months old.

Directions

Blend over entire face with fingertips.

Inactive Ingredients

water (aqua), cyclopentasiloxane, propylene, glycol, octyldodecyl neopentanoate, peg/ppg-18/18 dimethicone, dimethicone, cyclohexasiloxane, phytantriol, magnesium ascorbyl phosphate, retinyl palmitate, tocopheryl acetate, tocopherol, tetrahexyldecyl ascorbate, aluminum hydroxide, stearic acid, triethoxycaprylylsilane, boron nitride, glycerin, sodium dehydroacetate, palmitic acid, dextrin palmitate, sodium hyaluronate, butylene glycol, panax ginseng (ginseng) root extract, ginkgo biloba leaf extract, anthemis nobilis (chamomile) flower extract, camellia oleifera (camelia oleifera) leaf extract, magnesium chloride, potassium chloride, sodium chloride, zinc chloride, lysine, phenoxyethanol, hexylene glycol, caprylyl glycol, may contain (+/-): mica, titanium dioxide (ci 77891), iron oxides (ci 77491, ci 77492, ci 77499 <iln c101014r2>.

dist. by © stila styles, llc
los angeles, ca 90027

PRINCIPAL DISPLAY PANEL - 50 ml Tube Label

stila

bronzing
tinted moisturizer

oil-free

SPF 20

1.7 fl. oz./oz. liq./50 ml e